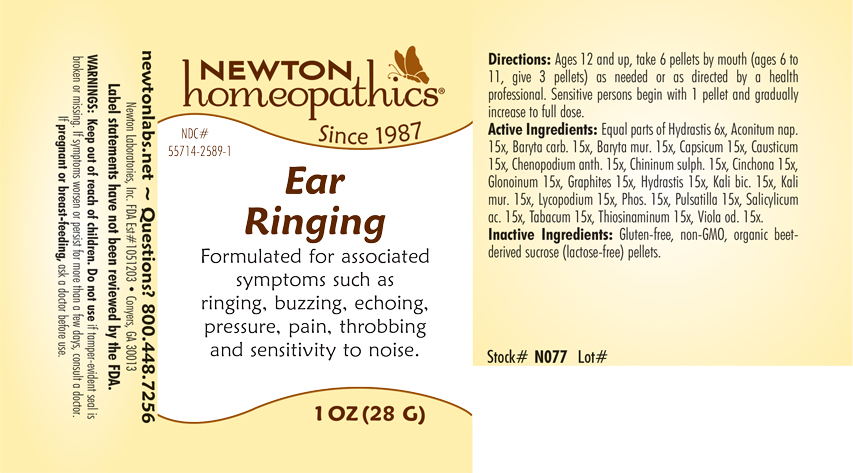 DRUG LABEL: Ear Ringing
NDC: 55714-2589 | Form: PELLET
Manufacturer: Newton Laboratories, Inc.
Category: homeopathic | Type: HUMAN OTC DRUG LABEL
Date: 20240131

ACTIVE INGREDIENTS: LYCOPODIUM CLAVATUM SPORE 15 [hp_X]/1 g; PHOSPHORUS 15 [hp_X]/1 g; PULSATILLA VULGARIS 15 [hp_X]/1 g; SALICYLIC ACID 15 [hp_X]/1 g; TOBACCO LEAF 15 [hp_X]/1 g; ALLYLTHIOUREA 15 [hp_X]/1 g; VIOLA ODORATA 15 [hp_X]/1 g; ACONITUM NAPELLUS 15 [hp_X]/1 g; BARIUM CARBONATE 15 [hp_X]/1 g; BARIUM CHLORIDE DIHYDRATE 15 [hp_X]/1 g; CAPSICUM 15 [hp_X]/1 g; CAUSTICUM 15 [hp_X]/1 g; DYSPHANIA AMBROSIOIDES 15 [hp_X]/1 g; QUININE SULFATE 15 [hp_X]/1 g; CINCHONA OFFICINALIS BARK 15 [hp_X]/1 g; NITROGLYCERIN 15 [hp_X]/1 g; GRAPHITE 15 [hp_X]/1 g; GOLDENSEAL 15 [hp_X]/1 g; POTASSIUM DICHROMATE 15 [hp_X]/1 g; POTASSIUM CHLORIDE 15 [hp_X]/1 g
INACTIVE INGREDIENTS: SUCROSE

EarRi 2589P

INDICATIONS & USAGE SECTION

Formulated for associated symptoms such as ringing, buzzing, echoing, pressure, pain, throbbing and sensitivity to noise.

DOSAGE & ADMINISTRATION SECTION

Directions: Ages 12 and up, take 6 pellets by mouth (ages 6 to 11, give 3 pellets) as needed or as directed by a health professional. Sensitive persons begin with 1 pellet and gradually increase to full dose.

OTC - ACTIVE INGREDIENT SECTION

Equal parts of Htdrastis 6x, Aconitum nap. 15x, Baryta carb. 15x, Baryta mur. 15x, Capsicum 15x, Causticum 15x, Chenopodium anthelminticum 15x, Chininum sulphuricum 15x, Cinchona 15x, Glonoinum 15x, Graphites 15x, Hydrastis 15x, Kali bic. 15x, Kali mur.15x, Lycopodium 15x, Phosphorus 15x, Pulsatilla 15x, Salicylicum ac.15x, Tabacum 15x, Thiosinaminum 15x, Viola odorata 15x.

OTC - PURPOSE SECTION

Formulated for associated symptoms such as ringing, buzzing, echoing, pressure, pain, throbbing and sensitivity to noise.

INACTIVE INGREDIENT SECTION

Inactive Ingredients: Gluten-free, non-GMO, organic beet-derived sucrose (lactose-free) pellets.

QUESTIONS SECTION

newtonlabs.net - Questions? 1.800.448.7256

Newton Laboratories, Inc. FDA Est # 1051203 - Conyers, GA 30013

WARNINGS SECTION

WARNINGS: Keep out of reach of children. Do no use if tamper-evident seal is broken or missing. If symptoms worsen or persist for more than a few days, consult a doctor.

If pregnant or breast-feeding, ask a doctor before use.

OTC - PREGNANCY OR BREAST FEEDING SECTION

If pregnant or breast-feeding, ask a doctor before use.

OTC - KEEP OUT OF REACH OF CHILDREN SECTION

Keep our of reach of children.